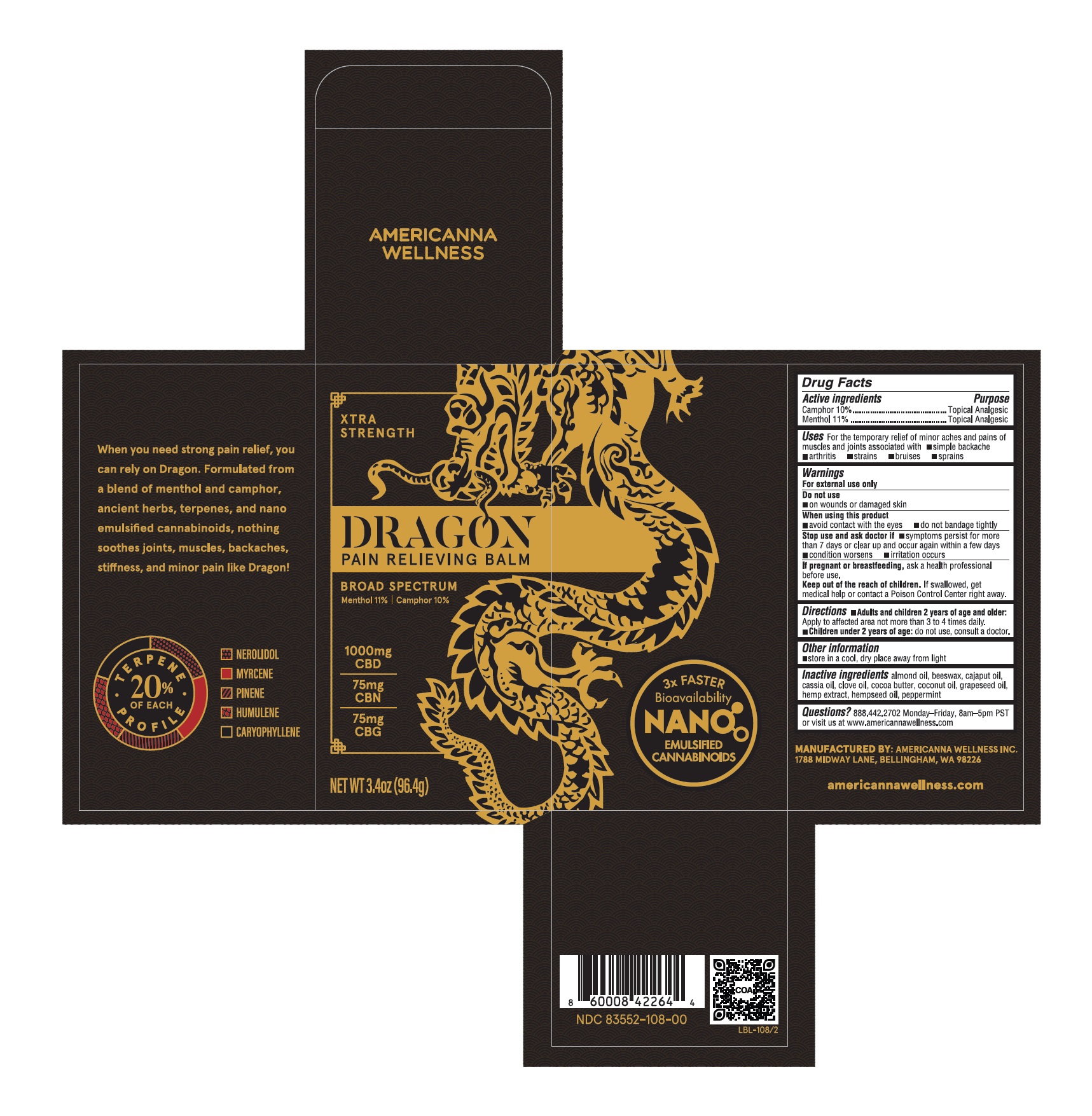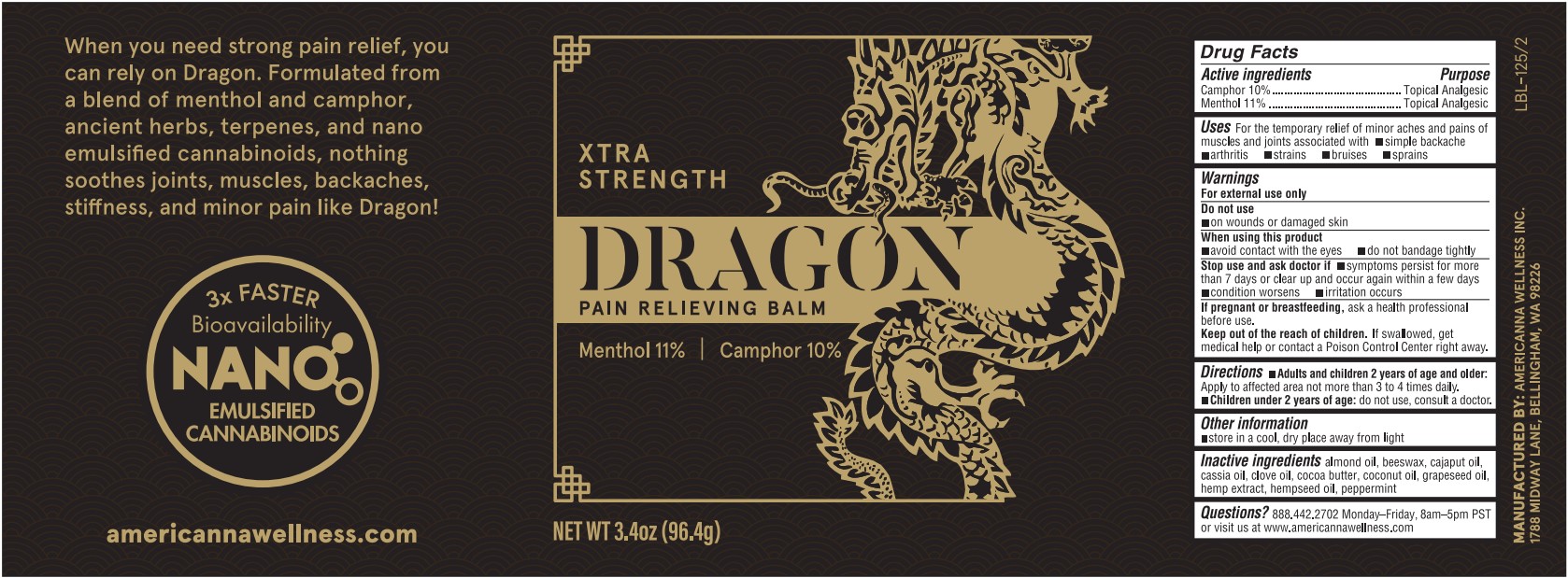 DRUG LABEL: Dragon Pain Relieving Balm
NDC: 83552-115 | Form: SALVE
Manufacturer: AMERICANNA WELLNESS, INC.
Category: otc | Type: HUMAN OTC DRUG LABEL
Date: 20251124

ACTIVE INGREDIENTS: CAMPHOR (SYNTHETIC) 10 g/100 g; MENTHOL 11 g/100 g
INACTIVE INGREDIENTS: CHINESE CINNAMON OIL; CLOVE OIL; GRAPE SEED OIL; CAJUPUT OIL; CANNABIS SATIVA SEED OIL; PEPPERMINT OIL; ALMOND OIL; YELLOW WAX; COCOA BUTTER; COCONUT OIL; HEMP

Dragon Pain Relieving Balm 3.4oz (XS BS)

Active ingredients

Camphor 10%

Menthol 11%

Purpose

Camphor 10%.................Topical Analgesic

Menthol 11%...................Topical Analgesic

Uses

For the temporary relief of minor aches and pains of muscles and joints associated with

- simple backache
- arthritis
- strains
- bruises
- sprains

Warnings

For external use only

Do not use

- on wounds or damaged skin

When using this product

- avoid contact with the eyes
- do not bandage tightly

When using this product

- avoid contact with the eyes
- do not bandage tightly

Stop use and ask doctor if

- symptoms persist for more than 7 days or clear up and occur again within a few days
- condition worsens
- irritation occurs

PREGNANCY OR BREAST FEEDING

If pregnant or breastfeeding, ask a health professional before use.

Keep out of reach of children.If swallowed, get medical help or contact a Poison Control Center right away.

Directions

- Adults and children 2 years of age and older:Apply to affected area not more than 3 to 4 times daily.
- Children under 2 years of age:do not use, consult a doctor.

Other information

- store in a cool, dry place away from light

Inactive ingredients

almond oil, beeswax, cajaput oil, cassia oil, clove oil, cocoa butter, coconut oil, grapeseed oil, hemp extract, hempseed oil, peppermint

Questions?

888.444.2702 Monday-Friday, 8am-5pm PST or visit us at www.americannawellness.com

PACKAGE LABEL

XTRA STRENGTH

DRAGON

PAIN RELIEVING BALM

BROAD SPECTRUM

Menthol 11%

Camphor 10%

1000mg CBD

75mg CBN

75mg CBG

NET WT. 3.4oz (96.4g)